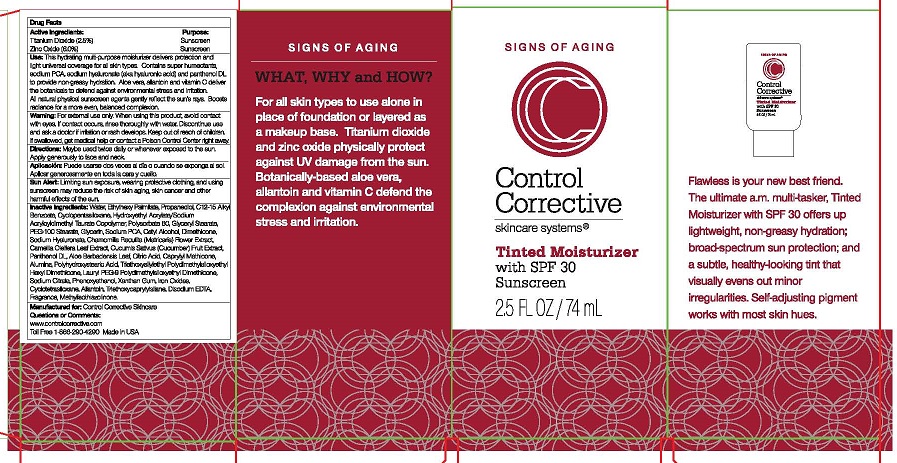 DRUG LABEL: CONTROL CORRECTIVE TINTED MOISTURIZER
NDC: 70764-206 | Form: CREAM
Manufacturer: CONTROL CORRECTIVE SKINCARE INC
Category: otc | Type: HUMAN OTC DRUG LABEL
Date: 20251231

ACTIVE INGREDIENTS: TITANIUM DIOXIDE 2.5 g/100 mL; ZINC OXIDE 6 g/100 mL
INACTIVE INGREDIENTS: ALKYL (C12-15) BENZOATE; CYCLOMETHICONE 5; HYDROXYETHYL ACRYLATE/SODIUM ACRYLOYLDIMETHYL TAURATE COPOLYMER (45000 MPA.S AT 1%); POLYSORBATE 60; GLYCERYL MONOSTEARATE; PEG-100 STEARATE; GLYCERIN; SODIUM PYRROLIDONE CARBOXYLATE; CETYL ALCOHOL; WATER; ETHYLHEXYL PALMITATE; PROPANEDIOL; DIMETHICONE; HYALURONATE SODIUM; MATRICARIA CHAMOMILLA FLOWERING TOP; CAMELLIA OLEIFERA LEAF; CUCUMIS SATIVUS WHOLE; PANTHENOL; ALOE VERA LEAF; ANHYDROUS CITRIC ACID; CAPRYLYL TRISILOXANE; ALUMINUM OXIDE; POLYHYDROXYSTEARIC ACID (2300 MW); LAURYL PEG-9 POLYDIMETHYLSILOXYETHYL DIMETHICONE; SODIUM CITRATE; PHENOXYETHANOL; XANTHAN GUM; FERRIC OXIDE RED; CYCLOMETHICONE 4; ALLANTOIN; TRIETHOXYCAPRYLYLSILANE; EDETATE DISODIUM

CONTROL CORRECTIVE TINTED MOISTURIZER WITH SPF 30 SUNSCREEN (70764-206)

ACTIVE INGREDIENTS

TITANIUM DIOXIDE (2.5%)

ZINC OXIDE (6.0%)

PURPOSE

SUNSCREEN

USE

THIS HYDRATING MULTI-PURPOSE MOISTURIZER DELIVERS PROTECTION AND LIGHT UNIVERSAL COVERAGE FOR ALL SKIN TYPES. CONTAINS SUPER HUMECTANTS, SODIUM PCA, SODIUM HYALURONATE (AKA HYALURONIC ACID) AND PANTHENOL DL TO PROIDE NON-GREASY HYDRATION. ALOE VERA, ALLANTOIN AND VITAMIN C DELIVER THE BOTANICALS TO DEFEND AGAINST ENVIRONMENTAL STRESS AND IRRITATION. ALL NATURAL PHYSICAL SUNSCREEN AGENTS GENTLY REFLECT THE SUN'S RAYS. BOOSTS RADIANCE FOR A MORE EVEN, BALANCED COMPLEXION.

WARNING

FOR EXTERNAL USE ONLY. WHEN USING THIS PRODUCT, AVOID CONTACT WITH EYES. IF CONTACT OCCURS, RINSE THOROUGHLY WITH WATER. DISCONTINUE USE AND ASK A DOCTOR IF IRRITATION OR RASH DEVELOPS.

DIRECTIONS

MAY BE USED TWICE DAILY OR WHENEVER EXPOSED TO THE SUN. APPLY GENEROUSLY TO FACE AND NECK.

OTHER SAFETY INFORMATION

SUN ALERT: LIMITING SUN EXPOSURE, WEARING PROTECTIVE CLOTHING, AND USING SUNSCREEN MAY REDUCE THE RISK OF SKIN AGING, SKIN CANCER, AND OTHER HARMFUL EFFECTS OF THE SUN.

INACTIVE INGREDIENTS

WATER, ETHYLHEXYL PALMITATE, PROPANEDIOL, C12-15 ALKYL BENZOATE, CYCLOPENTASILOXANE, HYDROXYETHYL ACRYLATE/SODIUM ACRYLOYLDIMETHYL TAURATE COPOLYMER, POLYSODBATE 60, GLYCERYL STEARATE, PEG-100 STEARATE, GLYCERIN, SODIUM PCA, CETYL ALCOHOL, DIMETHICONE, SODIUM HYALURONATE, CHAMOMILLA RECUTITIA (MATRICARIA) FLOWER EXTRACT, CAMELLIA OLEIFERA LEAF EXTRACT, CUCUMIS SATIVUS (CUCUMBER) FRUIT EXTRACT, PANTHENOL DL, ALOE BARBADENSIS LEAF, CITRIC ACID, CAPRYLYL METHICONE, ALUMINA, POLYHYDROXYSTEARIC ACID, TRIETHOXYSILYETHYL POLYDIMETHYLSILOXYETHYL HEXYL DIMETHICONE, LAYRYL PEG-9 POLYDIMETHYLSILOXYETHYL DIMETHICONE, SODIUM CITRATE, PHENOXYETHANOL, XANTHAN GUM, IRON OXIDES, CYCLOTETRASILOXANE, ALLANTOIN, TRIETHOCYCAPRYLYLSILANE, DISODIUM EDTA, FRAGRANCE, METHYLISOTHIAZOLINONE

KEEP OUT OF REACH OF CHILDREN. IF SWALLOWED, GET MEDICAL HELP OR CONTACT A POISON CONTROL CENTER RIGHT AWAY.

QUESTIONS OR COMMENTS:

WWW.CONTROLCORRECTIVE.COM

TOLL FREE 1-866-290-4290 MADE IN USA